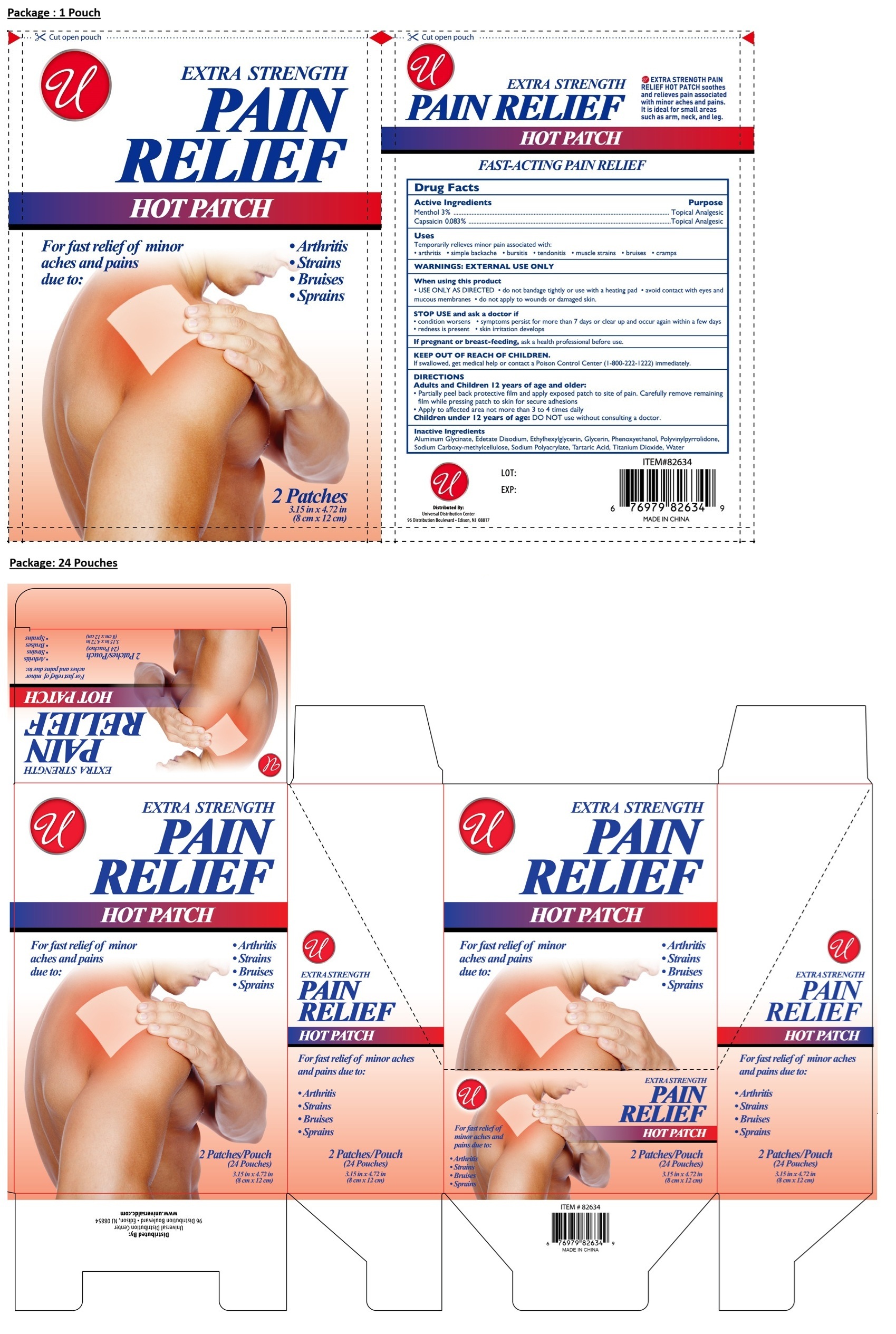 DRUG LABEL: Pain Relief Hot Patch
NDC: 52000-046 | Form: PATCH
Manufacturer: Universal Distribution Center LLC
Category: otc | Type: HUMAN OTC DRUG LABEL
Date: 20260106

ACTIVE INGREDIENTS: MENTHOL, UNSPECIFIED FORM 30 mg/1 g; CAPSAICIN 0.83 mg/1 g
INACTIVE INGREDIENTS: DIHYDROXYALUMINUM AMINOACETATE ANHYDROUS; EDETATE DISODIUM; ETHYLHEXYLGLYCERIN; GLYCERIN; PHENOXYETHANOL; POVIDONE K90; CARBOXYMETHYLCELLULOSE SODIUM, UNSPECIFIED; SODIUM POLYACRYLATE (2500000 MW); TARTARIC ACID; TITANIUM DIOXIDE; WATER

PAIN RELIEF HOT PATCH

Active Ingredients

Menthol 3%

Capsaicin 0.083%

Purpose

Topical Analgesic

Uses

Temporarily relieves minor pain associated with:

- arthritis • simple backache • bursitis • tendonitis • muscle strains • bruises • cramps

WARNINGS:

EXTERNAL USE ONLY

When using this product
• USE ONLY AS DIRECTED • do not bandage tightly or use with a heating pad • avoid contact with eyes and mucous membranes • do not apply to wounds or damaged skin.

STOP USE and ask a doctor if • condition worsens • symptoms persist for more than 7 days or clear up and occur again within a few days
• redness is present • skin irritation develops

If pregnant or breast-feeding, ask a health professional before use.

KEEP OUT OF REACH OF CHILDREN.

If swallowed, get medical help or contact a Poison Control Center (1-800-222-1222) immediately.

DIRECTIONS

Adults and Children 12 years of age and older:
• Partially peel back protective film and apply exposed patch to site of pain. Carefully remove remaining film while pressing patch to skin for secure adhesions
• Apply to affected area not more than 3 to 4 times daily

Children under 12 years of age: DO NOT use without consulting a doctor.

Inactive Ingredients

Aluminum Glycinate, Edetate Disodium, Ethylhexylglycerin, Glycerin, Phenoxyethanol, Polyvinylpyrrolidone, Sodium Carboxy-methylcellulose, Sodium Polyacrylate, Tartaric Acid, Titanium Dioxide, Water

For fast relief of minor aches and pains due to:
• Arthritis
• Strains
• Bruises
• Sprains

EXTRA STRENGTH PAIN RELIEF HOT PATCH soothes and relieves pain associated with minor aches and pains. It is ideal for small areas such as arm, neck and leg.

FAST-ACTING PAIN RELIEF

Distributed by:
Universal Distribution Center
96 Distribution Boulevard • Edison, NJ 08817

MADE IN CHINA